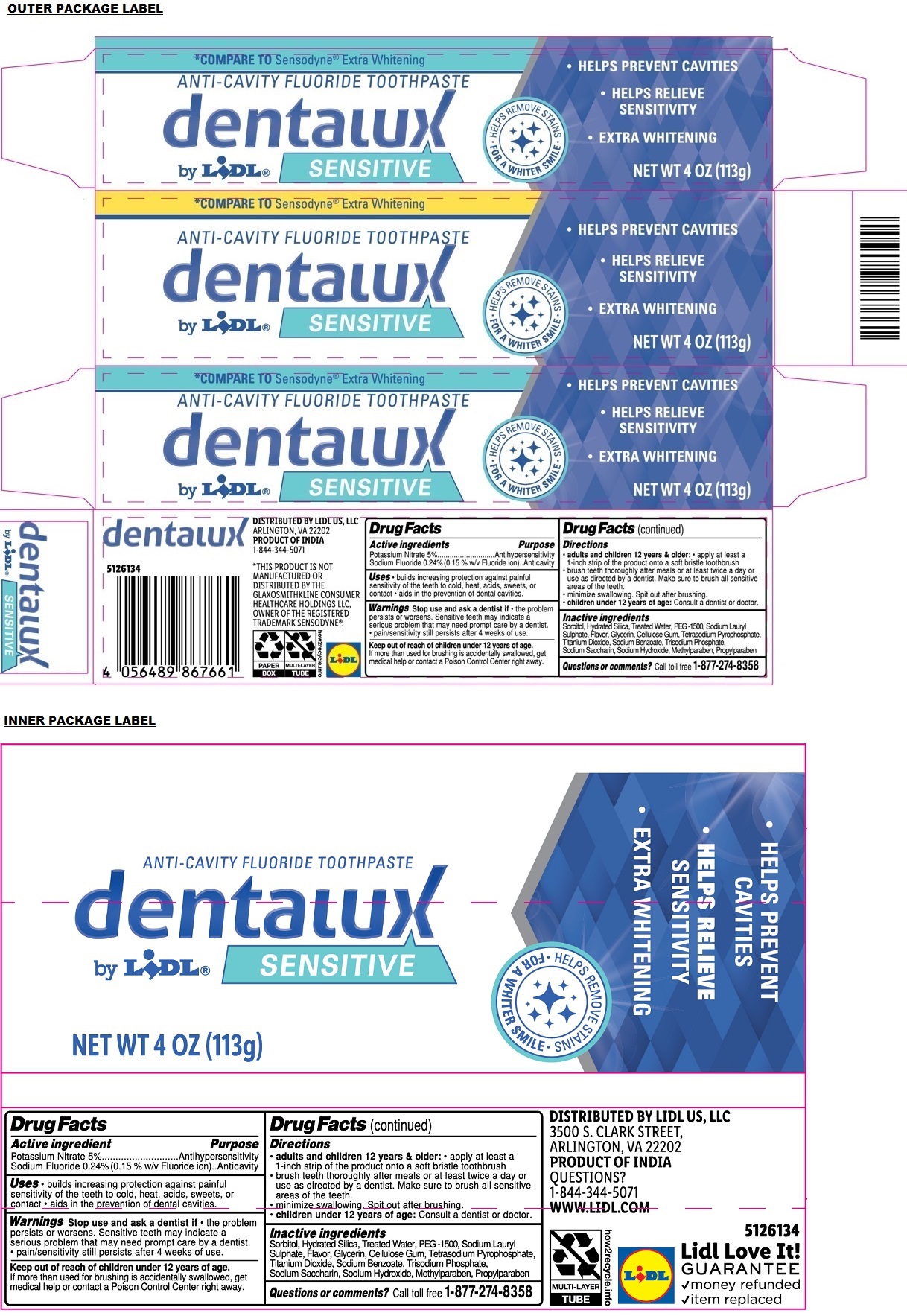 DRUG LABEL: dentalux SENSITIVE ANTI-CAVITY FLUORIDE
NDC: 71141-187 | Form: PASTE, DENTIFRICE
Manufacturer: Lidl US, LLC
Category: otc | Type: HUMAN OTC DRUG LABEL
Date: 20240703

ACTIVE INGREDIENTS: POTASSIUM NITRATE 5 g/100 g; SODIUM FLUORIDE 0.24 g/100 g
INACTIVE INGREDIENTS: SORBITOL; HYDRATED SILICA; WATER; POLYETHYLENE GLYCOL 1600; SODIUM LAURYL SULFATE; GLYCERIN; CARBOXYMETHYLCELLULOSE SODIUM, UNSPECIFIED; SODIUM PYROPHOSPHATE; TITANIUM DIOXIDE; SODIUM BENZOATE; SODIUM PHOSPHATE, TRIBASIC, ANHYDROUS; SACCHARIN SODIUM; SODIUM HYDROXIDE; METHYLPARABEN; PROPYLPARABEN

dentalux ANTI-CAVITY FLUORIDE TOOTHPASTE

Active ingredient

Potassium Nitrate 5%
Sodium Fluoride 0.24% (0.15% w/v Fluoride ion)

Purpose

Antihypersensitivity
Anticavity

Uses

• builds increasing protection against painful sensitivity of the teeth to cold, heat, acids, sweets, or contact • aids in the prevention of dental cavities.

Warnings

Stop use and ask a dentist if • the problem persists or worsens. Sensitive teeth may indicate a serious problem that may need prompt care by a dentist. • pain/sensitivity still persists after 4 weeks of use.

Keep out of reach of children under 12 years of age. If more than used for brushing is accidentally swallowed, get medical help or contact a Poison Control Center right away.

Directions

• adults and children 12 years & older: • apply at least a 1-inch strip of the product onto a soft bristle toothbrush
• brush teeth thoroughly after meals or at least twice a day or use as directed by a dentist. Make sure to brush all sensitive areas of the teeth.
• minimize swallowing. Spit out after brushing.
• children under 12 years of age: Consult a dentist or doctor.

Inactive ingredients

Sorbitol, Hydrated Silica, Treated Water, PEG-1500, Sodium Lauryl Sulphate, Flavor, Glycerin, Cellulose Gum, Tetrasodium Pyrophosphate, Titanium Dioxide, Sodium Benzoate, Trisodium Phosphate, Sodium Saccharin, Sodium Hydroxide, Methylparaben, Propylparaben

Questions or comments?

Call toll free 1-877-274-8358

*COMPARE TO Sensodyne® Extra Whitening

• HELPS PREVENT CAVITIES

• HELPS RELIEVE SENSITIVITY

• EXTRA WHITENING

HELPS REMOVE STAINS
FOR A WHITER SMILE

DISTRIBUTED BY LIDL US, LLC
3500 S. CLARK STREET,
ARLINGTON, VA 22202
PRODUCT OF INDIA
1-844-344-5071
WWW.LIDL.COM

*THIS PRODUCT IS NOT MANUFACTURED OR DISTRIBUTED BY THE GLAXOSMITHKLINE CONSUMER HEALTHCARE HOLDINGS LLC, OWNER OF THE REGISTERED TRADEMARK SENSODYNE®.

Lidl Love It!
GUARANTEE
✔money refunded
✓item replaced